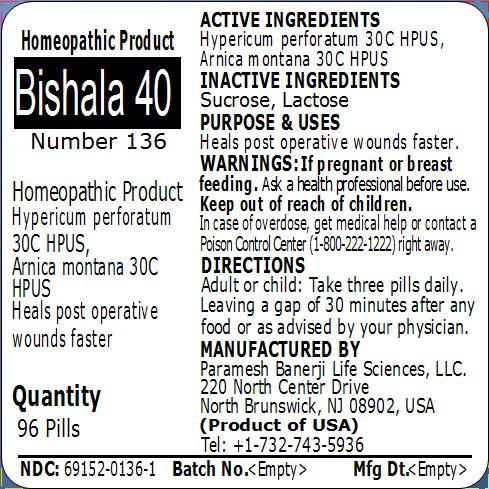 DRUG LABEL: Bishala 40 (Number 136)
NDC: 69152-0136 | Form: PELLET
Manufacturer: Paramesh Banerji Life Sciences LLC
Category: homeopathic | Type: HUMAN OTC DRUG LABEL
Date: 20150304

ACTIVE INGREDIENTS: HYPERICUM PERFORATUM 30 [hp_C]/1 1; ARNICA MONTANA 30 [hp_C]/1 1
INACTIVE INGREDIENTS: SUCROSE; LACTOSE

Active Ingredients

Hypericum perforatum 30C HPUS, Arnica montana 30C HPUS

Inactive Ingredients

Sucrose, Lactose

Purpose

Heals post operative wounds faster

Uses

Heals post operative wounds faster

Warnings

If pregnant or breast feeding ask a health professional before use.

Keep out of reach of children. In case of overdose, get medical help or contact a Poison Control Center (1-800-222-1222) right away.

Direction

Adult or child: Take three pills daily. Leaving a gap of 30 minutes after any food or as advised by your physician.

Manufactured by

Paramesh Banerji Life Sciences, LLC

220 North Center Drive

North Brunswick, NJ 08902, USA

Product of USA

Tel: +1-732-743-5936

Principal Display Panel

Homeopathic Product

Bishala 40

Number 136

Homeopathic Product

Hypericum perforatum 30C HPUS, Arnica montana 30C HPUS

Heals post operative wounds faster

Quantity

96 Pills